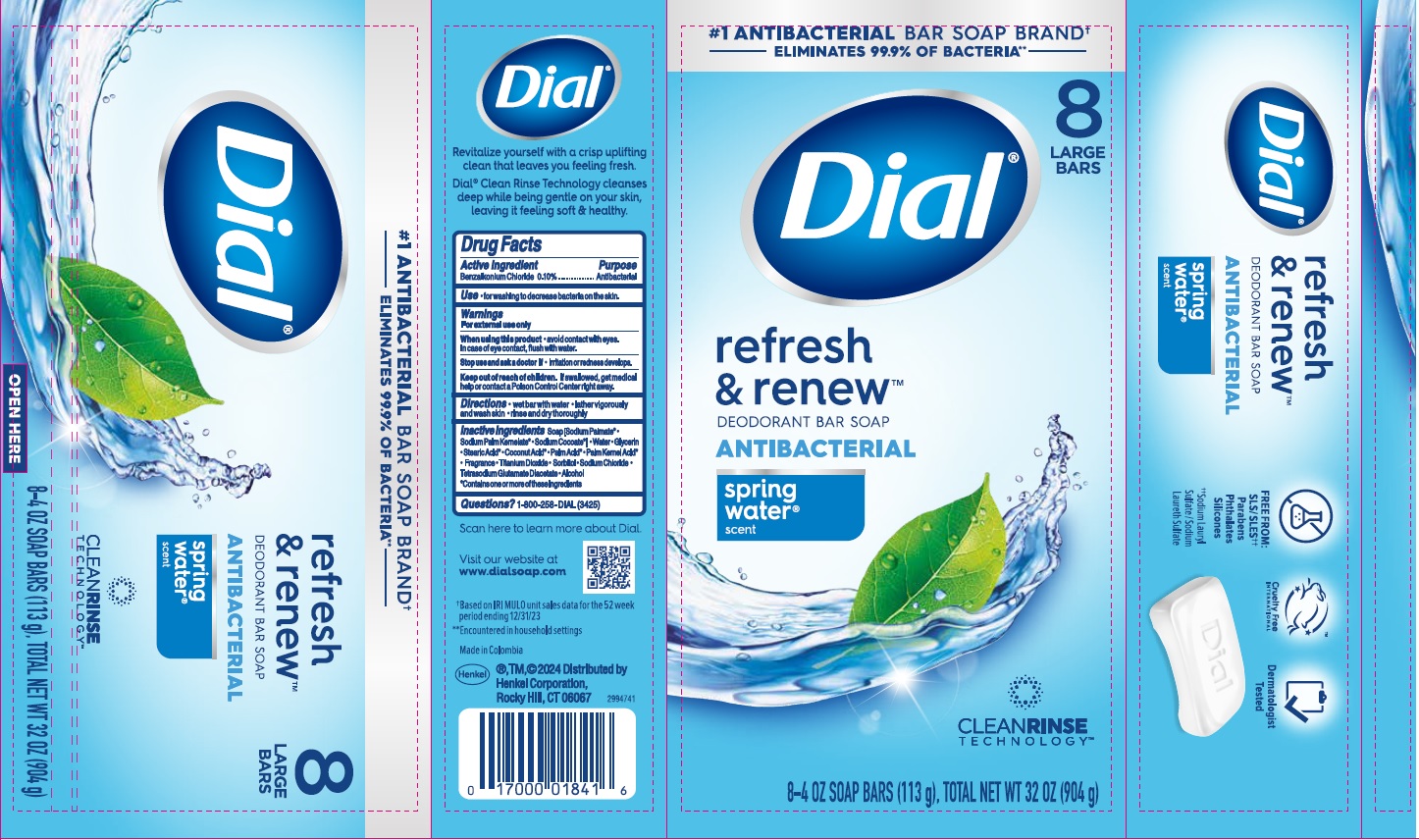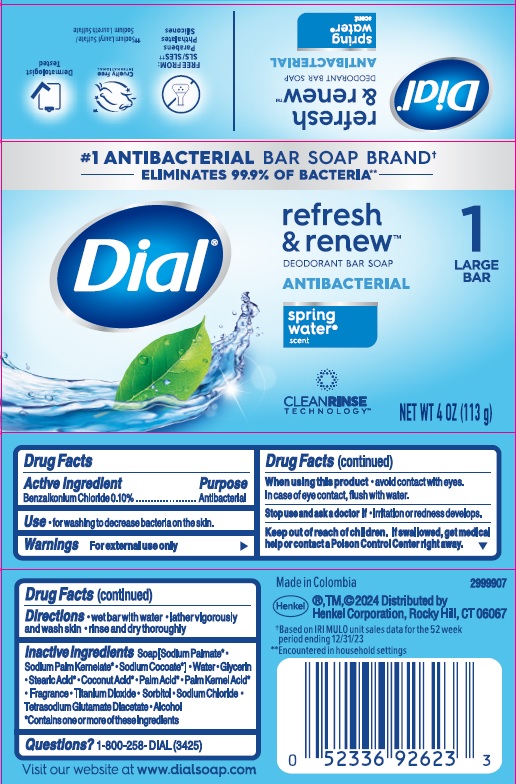 DRUG LABEL: Dial refresh and renew Antibacterial Bar
NDC: 54340-300 | Form: SOAP
Manufacturer: Henkel Corporation
Category: otc | Type: HUMAN OTC DRUG LABEL
Date: 20241120

ACTIVE INGREDIENTS: BENZALKONIUM CHLORIDE 0.1 g/100 g
INACTIVE INGREDIENTS: SODIUM PALMATE; SODIUM COCOATE; COCONUT ACID; STEARIC ACID; SORBITOL; TETRASODIUM GLUTAMATE DIACETATE; PALM ACID; GLYCERIN; WATER; PALM KERNEL ACID; ALCOHOL; TITANIUM DIOXIDE; SODIUM CHLORIDE; SODIUM PALM KERNELATE

Dial refresh & renew Antibacterial Soap - Spring Water

Drug Facts

Active ingredient

Benzalkonium Chloride 0.10%

Purpose

Antibacterial

Use

For washing to decrease bacteria on the skin.

Warnings

For external use only

When using this product • avoid contact with the eyes. In case of eye contact, flush with water.

Stop use and ask a doctor if • irritation and redness develops.

Keep out of reach of children. If swallowed, get medical help or contact a Poison Control Center right away.

DOSAGE AND ADMINISTRATION

Directions • wet bar with water • lather vigorously and wash skin • rinse and dry thoroughly

INACTIVE INGREDIENT

Inactive ingredients Soap (Sodium Palmate* • Sodium Palm Kernelate*• Sodium Cocoate*) • Water • Glycerin • Stearic Acid* • Coconut Acid* • Palm Acid* • Palm Kernel Acid* • Fragrance • Titanium Dioxide • Sorbitol • Sodium Chloride • Tetrasodium Glutamate Diacetate • Alcohol

*Contains one or more of these ingredients

Questions? 1-800-258-DIAL (3425)

Visit our website at www.dialsoap.com

Made in Colombia

Henkel®, TM, ©2024 Distributed by

Henkel Corporation, Rocky Hill, CT 06067

PACKAGE LABEL

Dial refresh & renew™

DEODORANT BAR SOAP

Antibacterial

spring water® scent